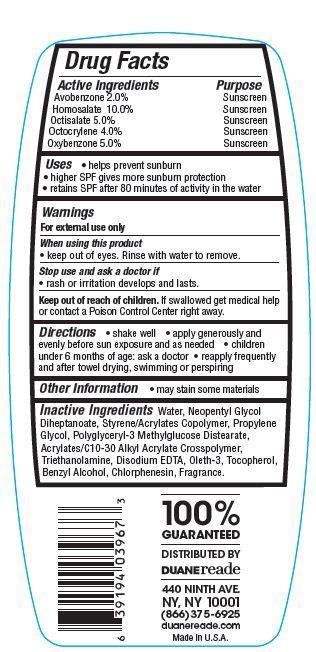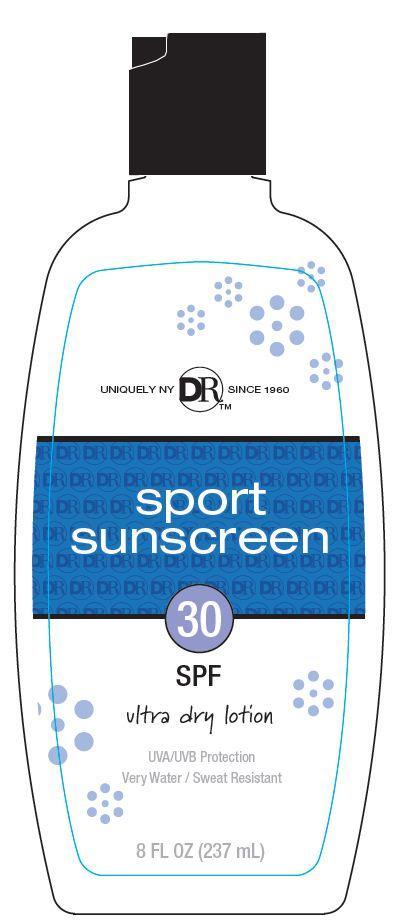 DRUG LABEL: Duane Reade Sports Sunscreen
NDC: 67732-405 | Form: LOTION
Manufacturer: DUANE READE INC.
Category: otc | Type: HUMAN OTC DRUG LABEL
Date: 20121113

ACTIVE INGREDIENTS: AVOBENZONE 2 g/100 g; HOMOSALATE 10 g/100 g; OCTISALATE 5 g/100 g; OCTOCRYLENE 4 g/100 g; OXYBENZONE 5 g/100 g
INACTIVE INGREDIENTS: WATER; SORBITOL; STEARIC ACID; TROLAMINE; ALUMINUM STARCH OCTENYLSUCCINATE; BENZYL ALCOHOL; SORBITAN ISOSTEARATE; DIMETHICONE; POLYGLYCERYL-3 DIISOSTEARATE; METHYLPARABEN; PROPYLPARABEN; TOCOPHEROL; EDETATE DISODIUM

Drug Facts

Active Ingredients

Avobenzone 2.0 %

Homosalate 10.0%

Octisalate 5.0%

Octocrylene 4.0%

Oxybenzone 5.0%

Purpose

Sunscreen

Uses

- helps prevent sunburn
- higher SPF gives more sunburn protection
- retains SPF after 80 minutes of activity in the water

Warnings

For external use only

When using this product

- keep out of eyes. Rinse with water to remove.

stop use and ask a doctor if

- rash or irritation develops and lasts

Keep out of reach of children.

If swallowed get medical help or contact a Poison Control Center right away.

Directions

- shake well
- apply generously before sun exposure and as needed
- Children under 6 months of age:ask a doctor
- reapply frequently and after towel drying, swimming or perspiring.

Inactive Ingredients

Water, Neopentyl Glycol Diheptanoate, Styrene/Acrylates Copolymer, Propylene Glycol, Polyglyceryl-3 Methylglucose Distearate, Benzyl Alcohol, Acrylates/C10-30 Alkyl Acrylate Crosspolymer, Triethanolamine, Disodium EDTA, Oleth-3, Tocopherol, Chlorphenesin, Fragrance.

Principal Display Panel

UNIQUELY NY DRTM SINCE 1960

sport

sunscreen
30
SPF

ultra dry lotion

UVA/UBA Protection
Very water /Sweat Resistant

8 FL OZ (237 mL)